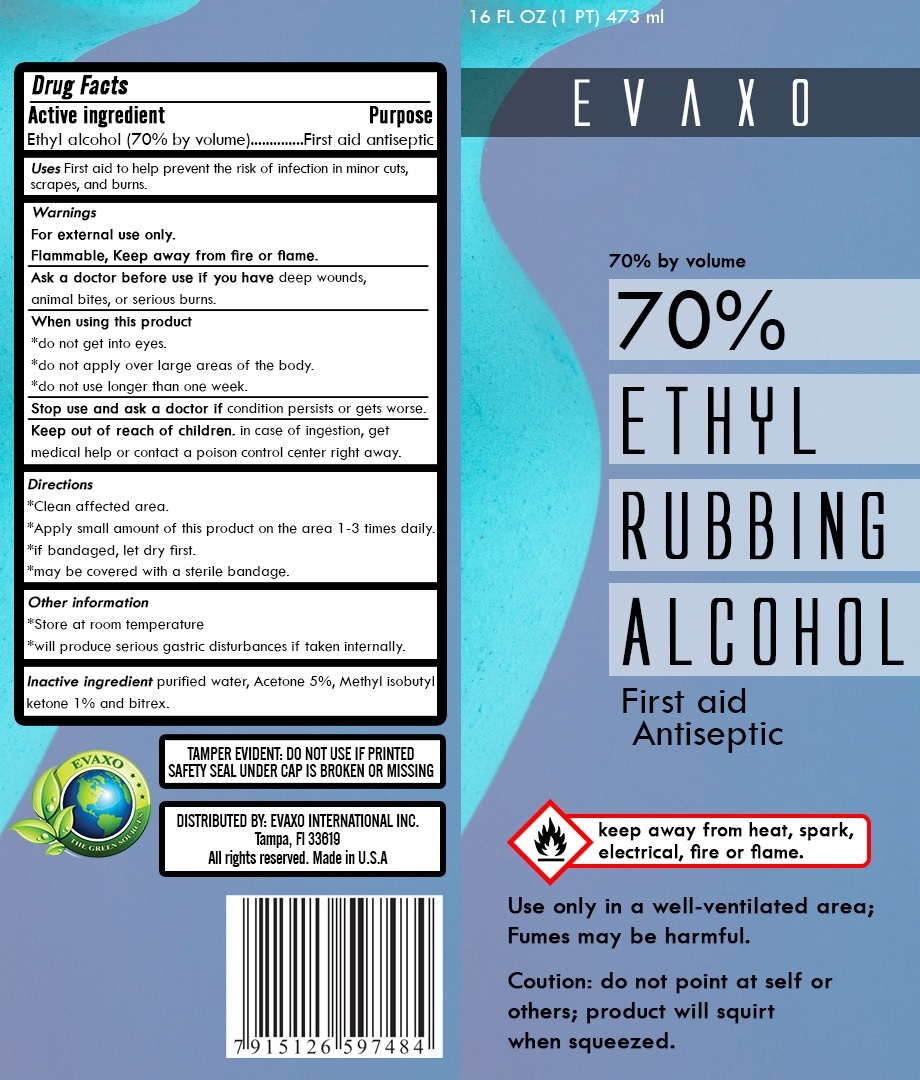 DRUG LABEL: Evaxo 70% Ethyl Rubbing alcohol
NDC: 78376-235 | Form: LIQUID
Manufacturer: Evaxo International Inc
Category: otc | Type: HUMAN OTC DRUG LABEL
Date: 20200602

ACTIVE INGREDIENTS: ALCOHOL 70 mL/100 mL
INACTIVE INGREDIENTS: WATER; ACETONE; METHYL ISOBUTYL KETONE; DENATONIUM BENZOATE

EVAXO 70% ETHYL RUBBING ALCOHOL

Active ingredient

Ethyl alcohol (70% by volume)

Purpose

First aid antiseptic

INDICATIONS AND USAGE

Uses First aid to help prevent the risk of infection in minor cuts, scrapes, and burns.

Warnings

For external use only.

Flammable, Keep away from fire or flame.

Ask a doctor before use if you have deep wounds, animal bites, or serious burns

When using this product

*do not get into eyes.

*do not apply over large areas of the body.

*do not use longer than one week.

Stop use and ask a doctor if condition persists or gets worse.

Keep out of reach of children. in case of ingestion, get medical help or contact a poison control center right away.

Directions

*Clean affected area.

*Apply small amount of this product on the area 1-3 times daily.

*if bandaged, let dry first.

*may be covered with a sterile bandage.

Other information

*Store at room temperature

*will produce serious gastric disturbances if taken internally.

Inactive ingredient purified water, Acetone 5%, Methyl isobutyl Ketone 1% and bitrex.

keep away from heat, spark, electrical, fire or flame.

Use only in a well-ventilated area;

Fumes may be harmful.

Caution: do not point at self or others; product will squirt when squeezed.

THE GREEN SOURCES

TAMPER EVIDENT: DO NOT USE IF PRINTED SAFETY SEAL UNDER CAP IS BROKEN OR MISSING

DISTRIBUTED BY: EVAXO INTERNATIONAL INC.

Tampa, FI 33619

All rights reserved. Made in U.S.A